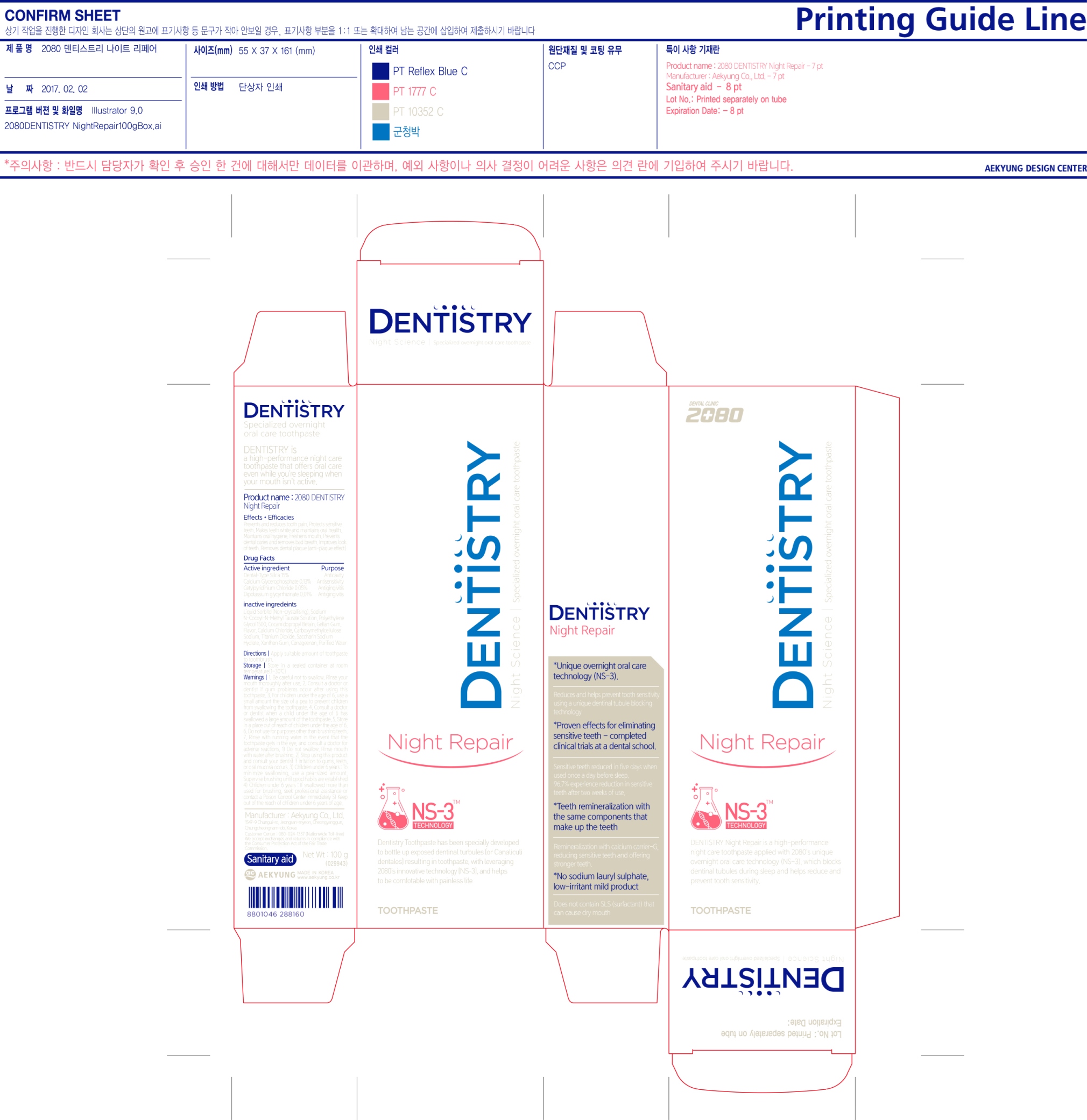 DRUG LABEL: 2080 Dentistry Night Repair
NDC: 67225-0010 | Form: PASTE, DENTIFRICE
Manufacturer: Aekyung Industrial Co., Ltd.
Category: otc | Type: HUMAN OTC DRUG LABEL
Date: 20170203

ACTIVE INGREDIENTS: SILICON DIOXIDE 15 g/100 g
INACTIVE INGREDIENTS: CETYLPYRIDINIUM CHLORIDE; CALCIUM GLYCEROPHOSPHATE; GLYCYRRHIZINATE DIPOTASSIUM; SORBITOL; SODIUM METHYL COCOYL TAURATE; POLYETHYLENE GLYCOL 1500; COCAMIDOPROPYL BETAINE; CARBOXYMETHYLCELLULOSE SODIUM; SACCHARIN SODIUM; GELLAN GUM (LOW ACYL); CALCIUM CHLORIDE; TITANIUM DIOXIDE; XANTHAN GUM; CARRAGEENAN; WATER

Drug Facts

ACTIVE INGREDIENT

Active Ingredients | Purpose
Dental-Type Silica 15% | Anticavity
Calcium Glycerophosphate 0.13% | Antisensitivity
Cetylpyridinium Chloride 0.05% | Antigingivitis
Dipotassium Glycyrrhizinate 0.01% | Antigingivitis

WARNINGS

Be careful not to swallow. Rinse your mouth thoroughly after use. Consult a doctor or dentist if gum problems occur after using this toothpaste.

KEEP OUT OF REACH OF CHILDREN

Keep out of the reach of children under 6 years of age

STOP USE

Stop using this product and consult your dentist if irritation to gums, teeth, or oral mucosa occurs

DOSAGE AND ADMINISTRATION

Do not swallow. Rinse mouth with water after brushing.

Children under 6 years:

- To minimize swallowing, use a pea-sized amount. Supervise brushing until good habits are established.

- If swallowed more than used for brushing, seek professional assistance or contact a Poison Control Center immediately.

INDICATIONS AND USAGE

- Prevents and reduces tooth pain

- Maintains oral hygiene

- Removes bad breath

- Prevents dental caries

INSTRUCTIONS FOR USE

Directions: Apply suitable amount of toothpaste to toothbrush

Do not use for purpose other than brushing teeth. Rinse with running water in the event that the toothpaste gets in the eye and consult a doctor for adverse reactions

STORAGE AND HANDLING

Store in a sealed container at room temperature {1~30°C}

QUESTIONS

Customer Center: 080-024-1357 (Nationwide Toll-Free)

We accept exchanges and returns in compliance with the Consumer Protection Act of the Fair Trade Commission

www.aekyung.co.kr

Manufacturer: Aekyung Co., Ltd

1547-9 Chungui-ro, Jeongsan-myeon, Cheongyanggun, Chungcheongnam-do, Korea

INACTIVE INGREDIENT

Inactive Ingredients: Liquid Sorbitol (Non-crystalizing), Sodium N-Cocoyl-N-Methyl Taurate Solution, Polyethylene Glycol 1500, Cocamidopropyl Betain, Gellan Gum, Flavor, Calcium Chloride, Carboxymethylcellulose Sodium, Titanium Dioxide, Saccharin Sodium Hydrate, Xanthan Gum, Carrageenan, Purified Water